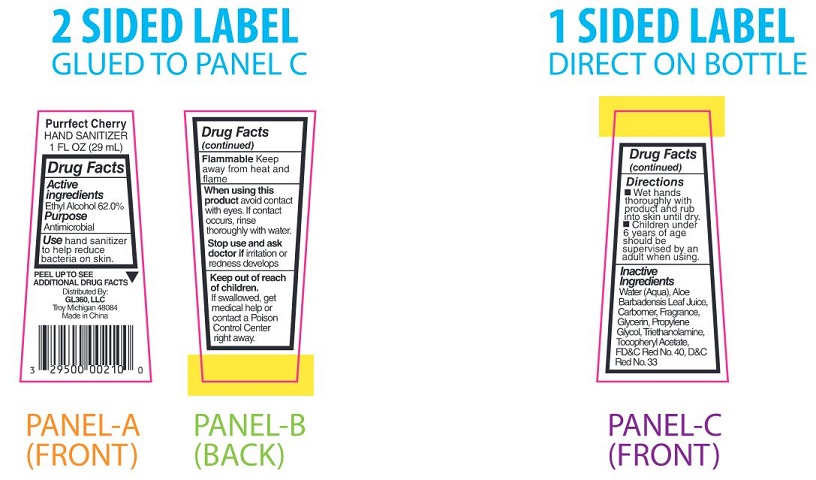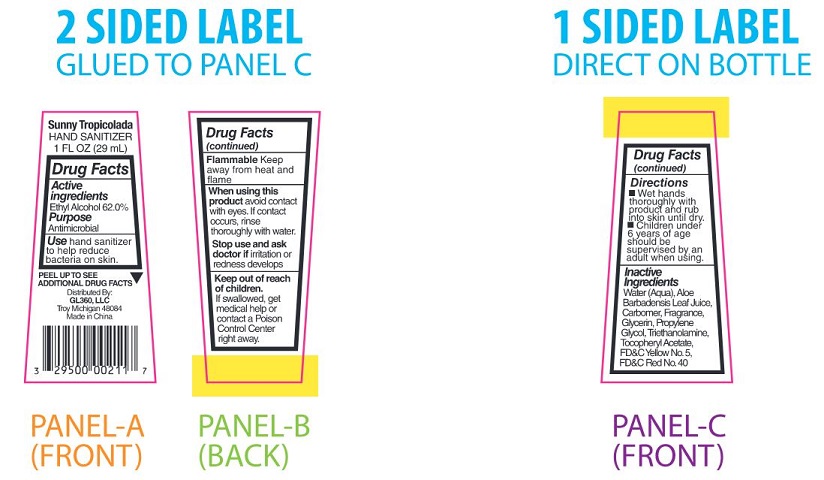 DRUG LABEL: Purrfect Cherry HAND SANITIZER
NDC: 29500-9826 | Form: LIQUID
Manufacturer: GL 360
Category: otc | Type: HUMAN OTC DRUG LABEL
Date: 20190213

ACTIVE INGREDIENTS: ALCOHOL 17.98 mL/29 mL
INACTIVE INGREDIENTS: WATER; ALOE VERA LEAF; CARBOXYPOLYMETHYLENE; GLYCERIN; PROPYLENE GLYCOL; TROLAMINE; .ALPHA.-TOCOPHEROL ACETATE; FD&C RED NO. 40; D&C RED NO. 33

HAND SANITIZER

Drug Facts

Active ingredients

Ethyl Alcohol 62.0%

Purpose

Antimicrobial

INDICATIONS AND USAGE

Use hand sanitizer
to help reduce
bacteria on skin.

WARNINGS

Flammable Keep
away from heat and flame

When using this
product avoid contact
with eyes. If contact
occurs, rinse
thoroughly with water.

Stop use and ask
doctor if irritation or
redness develops.

Keep out of reach
of children.
If swallowed, get
medical help or
contact a Poison
Control center
right away.

Directions
■ Wet hands
thoroughly with
product and rub
into skin until dry.
■ Children under
6 years of age
should be
supervised by an
adult when using.

Inactive
Ingredients
Water (Aqua), Aloe
Barbadensis Leaf
Juice, Carbomer,
Fragrance, Glycerin,
Propylene Glycol,
Triethanolamine,
Tocopheryl Acetate,
FD&C Red No. 40, D&C
Red No.33

Principal Display Package

Purrfect
Cherry
HAND SANITIZER
1 FL OZ (29 mL)

PEEL UP TO SEE
ADDITIONAL DRUG FACTS▼

Distributed By:
GL360, LLC
Troy Michigan, 48084
Made in China

↓Product Package↓

3 29500 00210 0

Sunny
Tropicolada
HAND SANITIZER
1 FL OZ (29 mL

PEEL UP TO SEE
ADDITIONAL DRUG FACTS▼

Distributed By:
GL360, LLC
Troy Michigan, 48084
Made in China

↓Product Package↓

3 29500 00211 7

res